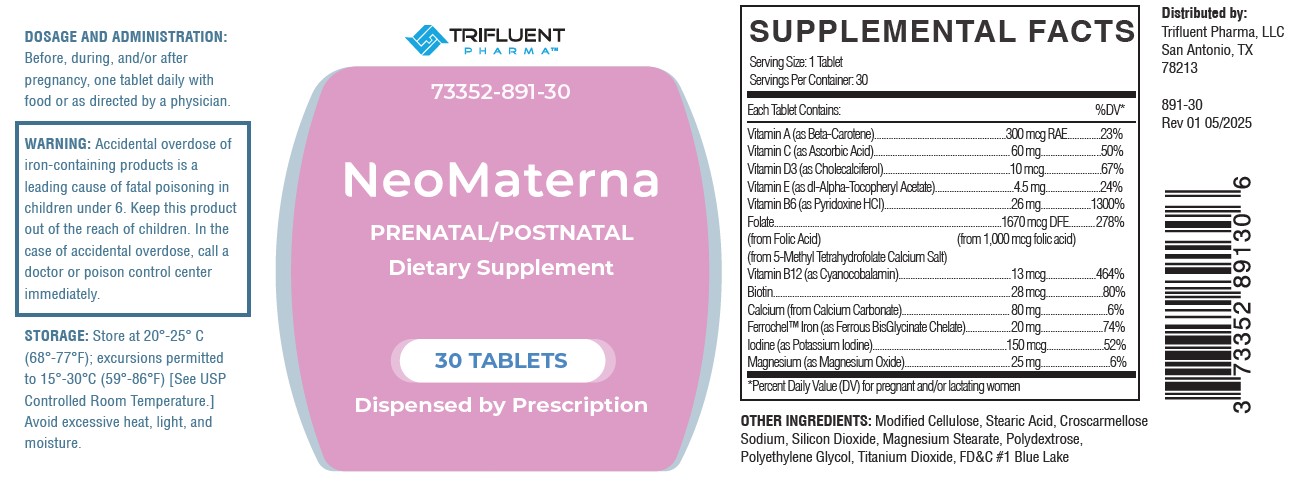 DRUG LABEL: NeoMaterna
NDC: 73352-891 | Form: TABLET
Manufacturer: Trifluent Pharma
Category: other | Type: DIETARY SUPPLEMENT
Date: 20250616

ACTIVE INGREDIENTS: ASCORBIC ACID 60 mg/1 1; BETA CAROTENE 300 ug/1 1; CHOLECALCIFEROL 10 ug/1 1; .ALPHA.-TOCOPHEROL ACETATE, DL- 4.5 mg/1 1; PYRIDOXINE HCL 26 mg/1 1; FOLIC ACID 1000 ug/1 1; LEVOMEFOLATE CALCIUM 670 ug/1 1; CYANOCOBALAMIN 13 ug/1 1; BIOTIN 28 ug/1 1; CALCIUM CARBONATE 80 mg/1 1; FERROUS BISGLYCINATE 20 mg/1 1; POTASSIUM IODIDE 150 ug/1 1; MAGNESIUM OXIDE 25 mg/1 1
INACTIVE INGREDIENTS: HYDROXYPROPYL CELLULOSE, UNSPECIFIED; STEARIC ACID; CROSCARMELLOSE SODIUM; SILICON DIOXIDE; MAGNESIUM STEARATE; TITANIUM DIOXIDE; POLYETHYLENE GLYCOL, UNSPECIFIED; POLYDEXTROSE; FD&C BLUE NO. 1

NeoMaterna
PRENATAL/POSTNATAL
Dietary Supplement

HEALTH CLAIM

NeoMaterna Prenatal/Postnatal Dietary Supplement - Dispensed by Prescription

STATEMENT OF IDENTITY

NeoMterna- beta carotene, ascorbic acid, cholecalciferol, dl-alpha-tocopheryl acetate, pyridoxine hydrochloride, folic acid, 5-methyl tetrahydrofolate, calcium salt, cyanocobalamin, biotin, calcium carbonate, ferrous bisglycinate, potassium iodine, and magnesium oxide tablet.

Serving Size: 1 Tablet; Servings Per Container: 30
Each Tablet Contains: |  | %DV
Vitamin A (as Beta-Carotene) | 300 mcg RAE | 23%
Vitamin C (as ascorbic acid) | 60 mg | 50%
Vitamin D3 (as cholecalciferol) | 10 mcg | 67%
Vitamin E (as dl-Alpha-Tocopheryl Acetate) | 4.5 mg | 24%
Vitamin B6 (as pyridoxine HCl) | 26 mg | 1300%
Folate; (From Folic Acid); (From 5-Methyl Tetrahydrofolate, Calcium Salt) | 1670 mcg DFE | 278%
Vitamin B12 (as Cyanocobalamine) | 13 mcg | 464%
Biotin | 28 mcg | 80%
Calcium (from Calcium Carbonate) | 80 mg | 6%
FerrochelTM Iron (as ferrous BisGlycinate Chelate) | 20 mg | 44%
Iodine (as potassium iodide) | 150 mcg | 52%
Magnesium (as Magnesium oxide) | 25 mg | 6%
* -Percent Daily Value for pregnant and/or lactating women

OTHER INGREDIENTS: Modified Cellulose, Stearic Acid, Croscarmellose Sodium, Silicon Dioxide, Magnesium Stearate, Polyethylene Glycol, Polydextrose, Titanium Dioxide, FD&C #1 Blue Lake

Allergen: NONE

DESCRIPTION

NeoMaterna is a prescription prenatal/postnatal multivitamin/ multimineral dietary supplement.

DOSAGE AND ADMINISTRATION

Before, during and/or after pregnancy, one tablet daily with food or as directed by a physician.

STORAGE

Store at 20°-25°C (68°-77°F) excursions permitted to 15°-30°C (59°-86°F) [See USP Controlled Room Temperature.] Avoid excessive heat, light
and moisture.

Distributed by:

Trifluent Pharma, LLC.

San Antonio, TX

78213

Rev 01 05/2025

WARNING

Accidental overdose of iron-containing products is a leading cause of fatal poisoning in Children under 6. Keep this product out of the reach of children. In the cse of acceidental overdose, call a docotr or poison control center immediately.